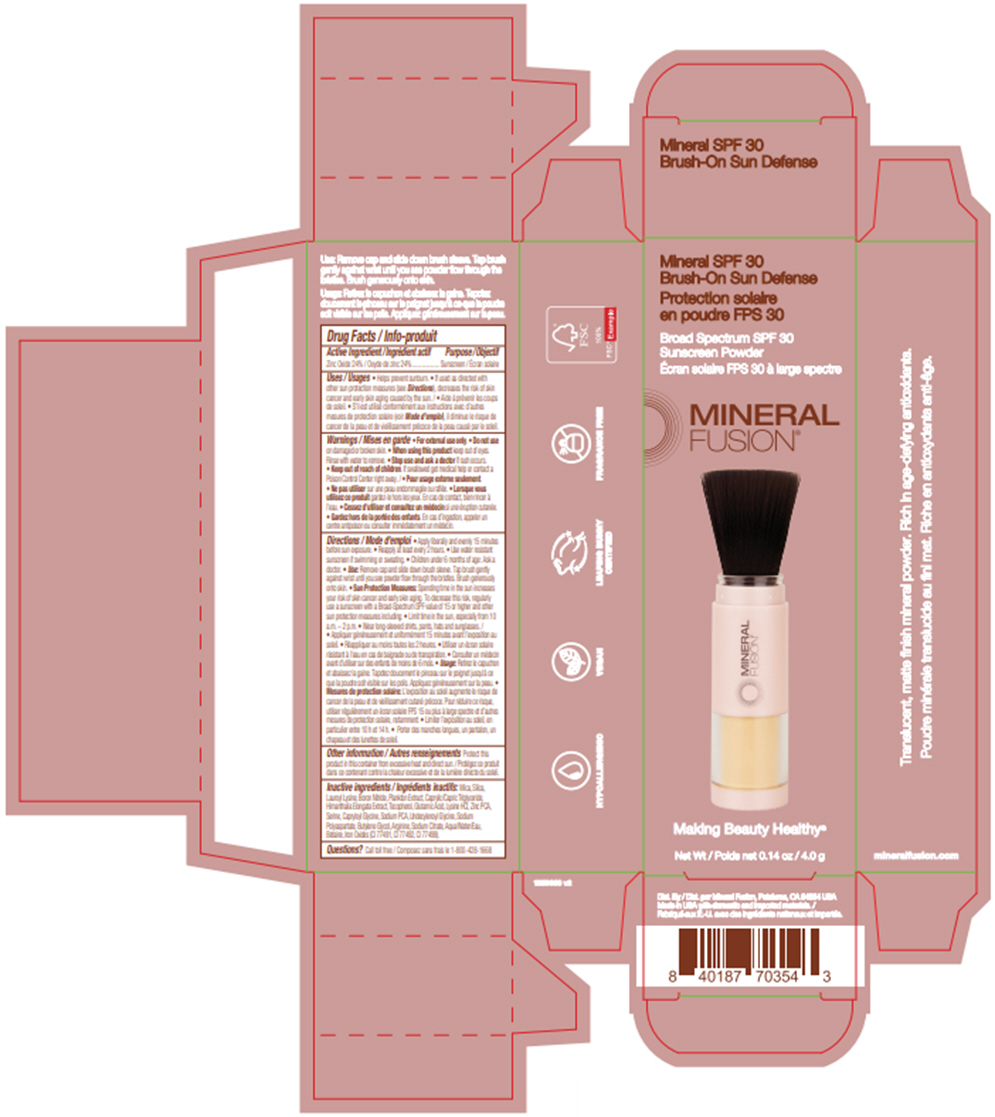 DRUG LABEL: Mineral SPF 30 Brush-On Sun Defense
NDC: 55789-1501 | Form: POWDER
Manufacturer: Mineral Fusion
Category: otc | Type: HUMAN OTC DRUG LABEL
Date: 20250219

ACTIVE INGREDIENTS: ZINC OXIDE 24 g/100 g
INACTIVE INGREDIENTS: MICA; SILICON DIOXIDE; Lauroyl Lysine; Boron Nitride; ALARIA ESCULENTA; MEDIUM-CHAIN TRIGLYCERIDES; HIMANTHALIA ELONGATA; TOCOPHEROL; GLUTAMIC ACID; LYSINE HYDROCHLORIDE; ZINC PIDOLATE; Serine; Capryloyl Glycine; SODIUM PYRROLIDONE CARBOXYLATE; Undecylenoyl Glycine; Butylene Glycol; Arginine; SODIUM CITRATE, UNSPECIFIED FORM; Water; Betaine; FERRIC OXIDE RED; FERRIC OXIDE YELLOW; FERROSOFERRIC OXIDE

Mineral SPF 30 Brush-On Sun Defense

Drug Facts

Active Ingredient

Zinc Oxide 24%

Purpose

Sunscreen

Uses

- Helps prevent sunburn.
- If used as directed with other sun protection measures (see Directions), decreases the risk of skin cancer and early skin aging caused by the sun.

Warnings

- For external use only.

- Do not use on damaged or broken skin.

- When using this product keep out of eyes. Rinse with water to remove.

- Stop use and ask a doctor if rash occurs.

- Keep out of reach of children. If swallowed get medical help or contact a Poison Control Center right away.

Directions

- Apply liberally and evenly 15 minutes before sun exposure.
- Reapply at least every 2 hours.
- Use water resistant sunscreen if swimming or sweating.
- Children under 6 months of age: Ask a doctor.
- Use: Remove cap and slide down brush sleeve. Tap brush gently against wrist until you see powder flow through the bristles. Brush generously onto skin.
- Sun Protection Measures: Spending time in the sun increases your risk of skin cancer and early skin aging. To decrease this risk, regularly use a sunscreen with a Broad-Spectrum SPF value of 15 or higher and other sun protection measures including:
  - Limit time in the sun, especially from 10 a.m. – 2 p.m.
  - Wear long-sleeved shirts, pants, hats and sunglasses.

Other information

Protect this product in this container from excessive heat and direct sun.

Inactive ingredients

Mica, Silica, Lauroyl Lysine, Boron Nitride, Plankton Extract, Caprylic/Capric Triglyceride, Himanthalia Elongata Extract, Tocopherol, Glutamic Acid, Lysine HCl, Zinc PCA, Serine, Capryloyl Glycine, Sodium PCA, Undecylenoyl Glycine, Sodium Polyaspartate, Butylene Glycol, Arginine, Sodium Citrate, Aqua/Water/Eau, Betaine, Iron Oxides (CI 77491, CI 77492, CI 77499).

Questions?

Call toll free 1-800-428-1668

Dist. By Mineral Fusion, Petaluma, CA 94954 USA

PRINCIPAL DISPLAY PANEL - 4.0 g Tube Carton

Mineral SPF 30
Brush-On Sun Defense

Broad Spectrum SPF 30
Sunscreen Powder

MINERAL
FUSION®

Making Beauty Healthy®

Net Wt 0.14 oz / 4.0 g